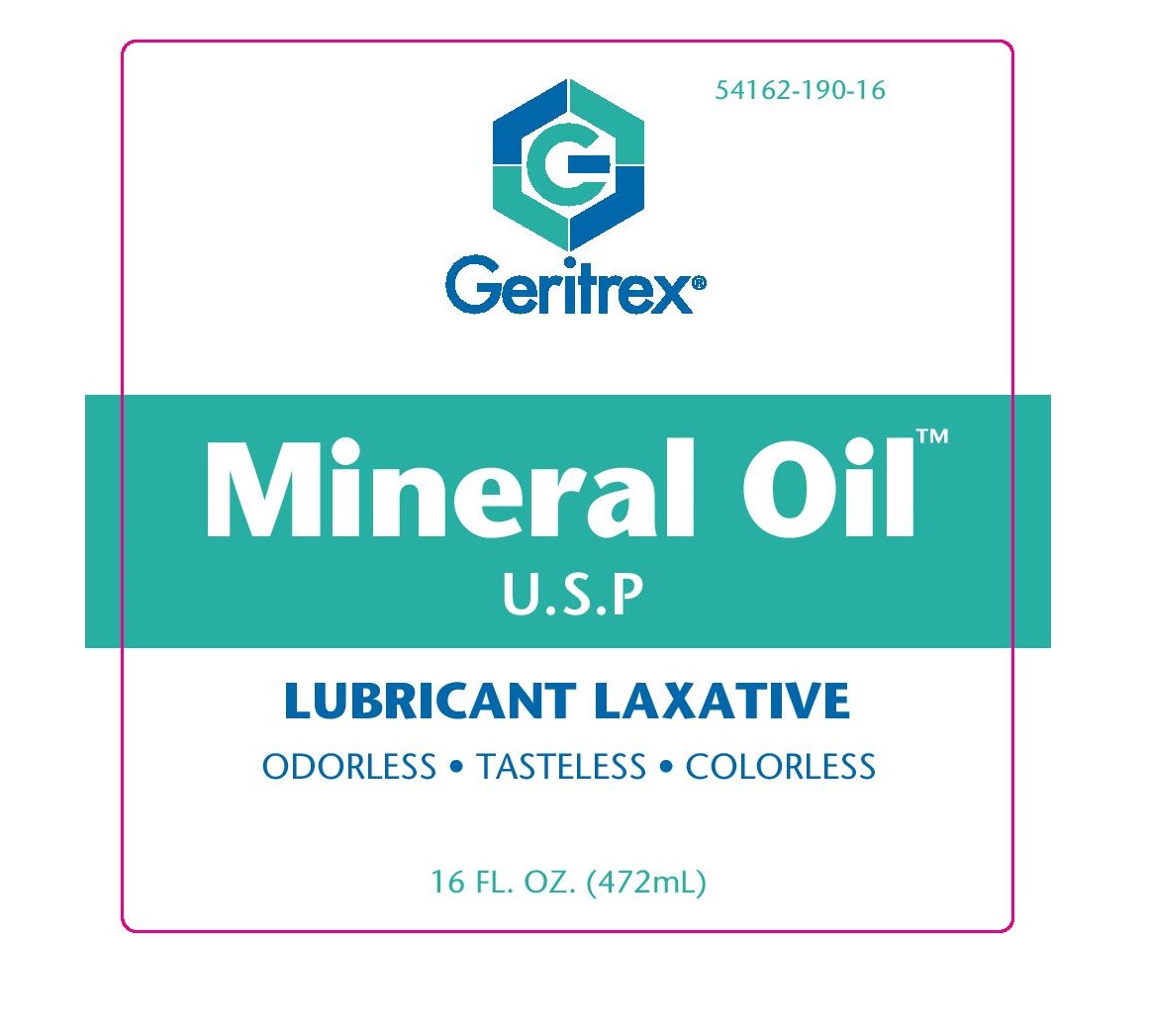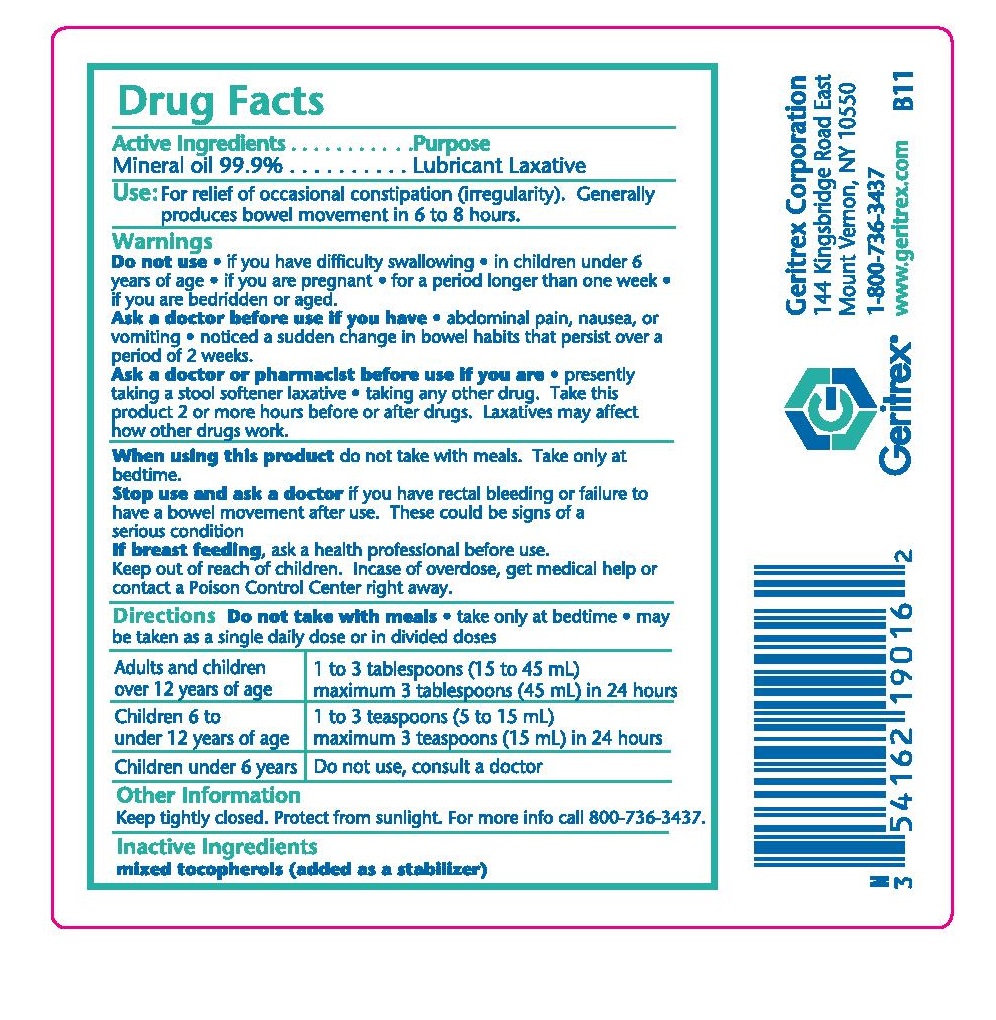 DRUG LABEL: Mineral Oil
NDC: 54162-190 | Form: OIL
Manufacturer: Geritrex LLC
Category: otc | Type: HUMAN OTC DRUG LABEL
Date: 20150731

ACTIVE INGREDIENTS: MINERAL OIL 471.9528 g/472 mL
INACTIVE INGREDIENTS: ALPHA-TOCOPHEROL

Mineral Oil

Active Ingredient

Mineral Oil 99.99%

Purpose:

Lubricant Laxative

Uses

For relief of occasional constipation (irregularity)

generally produces bowel movement in 6 to 8 hours

Warnings

Do not use

- if you have difficulty swallowing
- in children under 6 years of age
- if you are pregnant
- for a period longer than one week
- if you are bedridden or aged

Ask a doctor before use if you have

- abdominal pain, nausea or vomiting
- noticed a sudden change in bowel habits that persists over a period of 2 weeks

Ask a doctor of pharmamcist before use if you are

- Presently taking a stool softener laxative
- Taking any other drug
- Take this product 2 or more hours before or after drugs
- Laxatives may affect how other drugs work

When using this product

do not take with meals. take only at bedtime

Stop use and ask a doctor

If you have rectal bleeding or failure to have a bowel movement after use.

These could be signs of a serious condition

If pregnant or breast feeding,

ask a health professional before use.

Keep out of the reach of children

In case of accidental overdose, get medical help or contact a Poison Control Center right away

Directions

- Do not take with meals
- take only at bedtime
- may be taken as a single daily dose or in divided doses

Age Dose

adults and children over 12 years 1 to 3 tablespoons (15 to 45 ml)

maximum 3 tablespoons (45mL) in 24 hours

children 6 years to under 12 years 1 to 3 teaspoons(15 to 45 ml)

maximum 3 teaspoons (45mL) in 24 hours

Children under 6 years Do not use, consult a doctor

Other Information

Keep tightly closed. Protect from sunlight. For more info call 800-736-3437

Inactive Ingredients

Mixed tocopherols (added as a stabilizer)

Principal Display Panel

Geritrex

Mineral Oil

USP

Lubricant Laxative

Odorless

Tasteless

Colorless

16 OZ (472 ml)